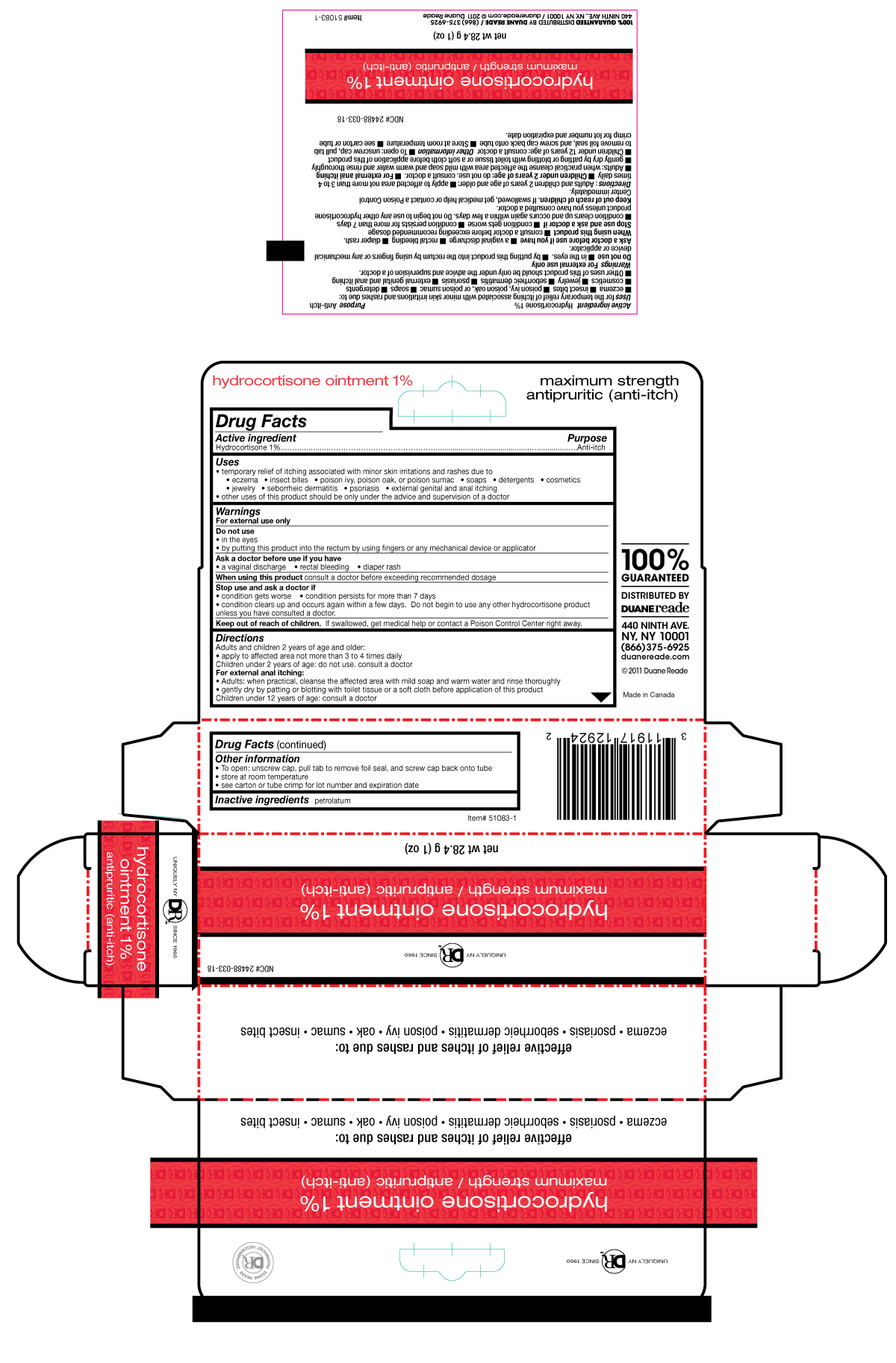 DRUG LABEL: Duane Reade
NDC: 24488-033 | Form: CREAM
Manufacturer: Duane Reade
Category: otc | Type: HUMAN OTC DRUG LABEL
Date: 20110318

ACTIVE INGREDIENTS: HYDROCORTISONE .284 g/28.4 g
INACTIVE INGREDIENTS: PETROLATUM

Drug Facts

Active Ingredients..........................Purpose

Hydrocortisone 1%..........................Anti-Itch

Uses

Temporary relief of itching associated with minor skin irritations and rashes due to

- eczema
- insect bites
- poison ivy, poison oak, or poison sumac
- soaps
- detergents
- cosmetics
- jewelry
- seborrheic dermatitis
- psoriasis
- external genital or anal itching

other uses of this product should be only under the advice and supervision of a doctor

Warnings

For external use only.

Do not use

- in the eyes
- by putting this product into the rectum by using fingers or any other mechanical device or applicator

Ask a doctor before use if you have

- a vaginal discharge
- rectal bleeding
- diaper rash

When using this product

consult a doctor before exceeding recommended dosage

Stop use and ask a doctor if

- condition gets worse
- condition persists for more than 7 days
- condition clears up and occurs again within a few days. Do not begin to use any other hydrocortisone product unless you have consulted a doctor.

Keep out of reach of children.

If swallowed, get medical help or contract a Poison Control Center right away.

Directions

Adults and children 2 years of age and older:

- apply to affected area not more than 3 to 4 times daily

Children under 2 years of age: do not use, consult a doctor

For external anal itching:

- Adults: when practical, cleanse the affected area with mild soap and warm water and rinse thoroughly
- gently dry by patting or blotting with toilet tissue or a soft cloth before application of this product.

Children under 12 years of age: consult a doctor

Other information

- To open: unscrew cap, pull tab to remove foil seal, and screw cap back onto tube
- store at room temperature
- see carton or tube crimp for lot number and expiration date

Inactive Ingredients

Petrolatum

PACKAGE LABEL

Placeholder text